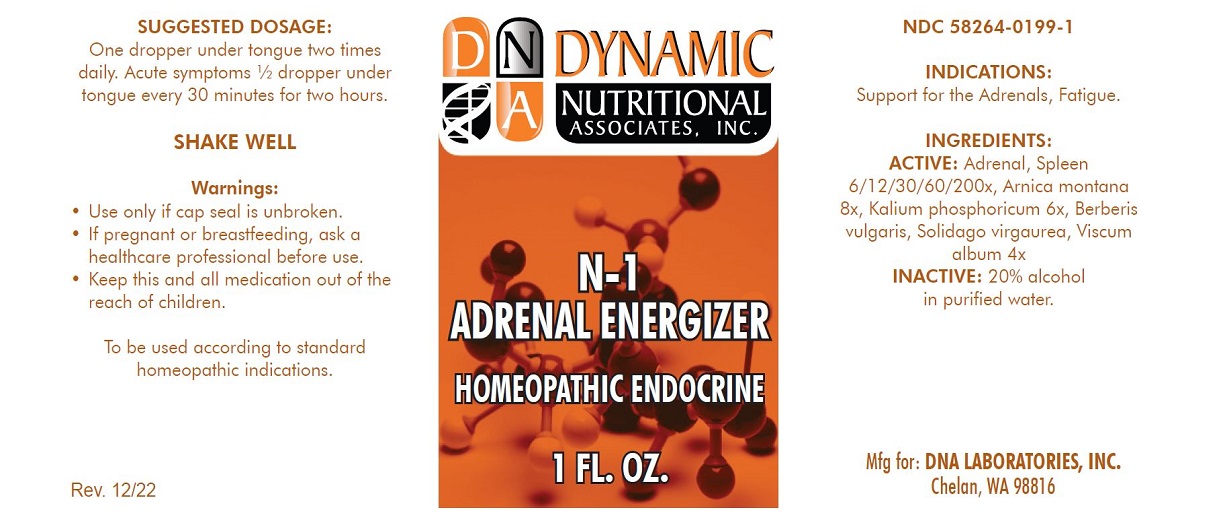 DRUG LABEL: N-1

NDC: 58264-0199 | Form: SOLUTION
Manufacturer: DNA Labs, Inc.
Category: homeopathic | Type: HUMAN OTC DRUG LABEL
Date: 20250109

ACTIVE INGREDIENTS: BERBERIS VULGARIS WHOLE 4 [hp_X]/1 mL; VISCUM ALBUM WHOLE 4 [hp_X]/1 mL; SOLIDAGO VIRGAUREA WHOLE 4 [hp_X]/1 mL; BOS TAURUS ADRENAL GLAND 200 [hp_X]/1 mL; ARNICA MONTANA 8 [hp_X]/1 mL; DIBASIC POTASSIUM PHOSPHATE 6 [hp_X]/1 mL; SUS SCROFA SPLEEN 200 [hp_X]/1 mL
INACTIVE INGREDIENTS: ALCOHOL; WATER

N-1

NDC 58264-0199-1

INDICATIONS AND USAGE

INDICATIONS

Support for the Adreanals, Fatigue.

ACTIVE INGREDIENT

INGREDIENTS

Adrenal, Spleen 6/12/30/60/200x, Arnica montana 8x, Kalium phosphoricum 6x, Berberis vulgaris, Solidago virgaurea, Viscum album 4x, 20% alcohol in purified water.

SUGGESTED DOSAGE

One dropper under tongue two times daily. Acute symptoms ½ dropper under tongue every 30 minutes for two hours.

STORAGE AND HANDLING

SHAKE WELL

Warnings

- Use only if cap seal is unbroken.

PREGNANCY OR BREAST FEEDING

- As with drugs if you are pregnant or nursing a baby seek professional advice before using this product.

KEEP OUT OF REACH OF CHILDREN

- Keep this and all medication out of the reach of children.

To be used according to standard homeopathic indications.

PRINCIPAL DISPLAY PANEL - 1 FL. OZ. Bottle Label

DYNAMIC
NUTRITIONAL
ASSOCIATES, INC.

N-1
ADRENAL ENERGIZER

HOMEOPATHIC ENDOCRINE

1 FL. OZ.